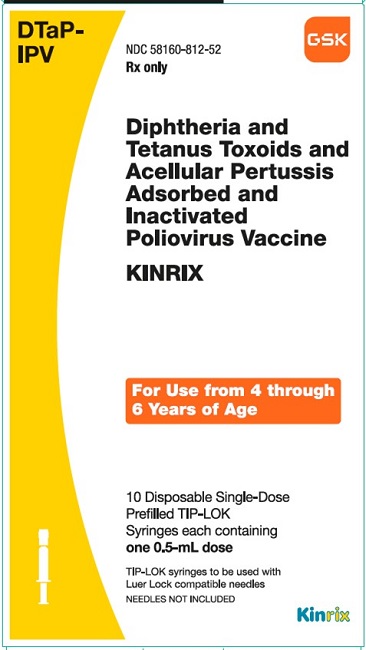 DRUG LABEL: KINRIX
NDC: 58160-812 | Form: INJECTION, SUSPENSION
Manufacturer: GlaxoSmithKline Biologicals SA
Category: other | Type: VACCINE LABEL
Date: 20241126

ACTIVE INGREDIENTS: CORYNEBACTERIUM DIPHTHERIAE TOXOID ANTIGEN (FORMALDEHYDE INACTIVATED) 25 [iU]/0.5 mL; CLOSTRIDIUM TETANI TOXOID ANTIGEN (FORMALDEHYDE INACTIVATED) 10 [iU]/0.5 mL; BORDETELLA PERTUSSIS FILAMENTOUS HEMAGGLUTININ ANTIGEN (FORMALDEHYDE INACTIVATED) 25 [iU]/0.5 mL; BORDETELLA PERTUSSIS PERTACTIN ANTIGEN (FORMALDEHYDE INACTIVATED) 8 ug/0.5 mL; BORDETELLA PERTUSSIS TOXOID ANTIGEN (FORMALDEHYDE, GLUTARALDEHYDE INACTIVATED) 25 ug/0.5 mL; POLIOVIRUS TYPE 1 ANTIGEN (FORMALDEHYDE INACTIVATED) 40 [iU]/0.5 mL; POLIOVIRUS TYPE 2 ANTIGEN (FORMALDEHYDE INACTIVATED) 8 [iU]/0.5 mL; POLIOVIRUS TYPE 3 ANTIGEN (FORMALDEHYDE INACTIVATED) 32 [iU]/0.5 mL
INACTIVE INGREDIENTS: ALUMINUM HYDROXIDE; FORMALDEHYDE; NEOMYCIN SULFATE; POLYMYXIN B; POLYSORBATE 80; SODIUM CHLORIDE

HIGHLIGHTS OF PRESCRIBING INFORMATION

These highlights do not include all the information needed to use KINRIX safely and effectively. See full prescribing information for KINRIX.
KINRIX (Diphtheria and Tetanus Toxoids and Acellular Pertussis Adsorbed and Inactivated Poliovirus Vaccine) Suspension for Intramuscular Injection
Initial U.S. Approval: 2008

1 INDICATIONS AND USAGE

A single dose of KINRIX is indicated for active immunization against diphtheria, tetanus, pertussis, and poliomyelitis as the fifth dose in the diphtheria, tetanus, and acellular pertussis (DTaP) vaccine series and the fourth dose in the inactivated poliovirus vaccine (IPV) series in children aged 4 through 6 years (prior to the seventh birthday) whose previous DTaP vaccine doses have been with INFANRIX and/or PEDIARIX for the first 3 doses and INFANRIX for the fourth dose. (1)

2 DOSAGE AND ADMINISTRATION

A single intramuscular injection (0.5 mL). (2.2)

3 DOSAGE FORMS AND STRENGTHS

Single-dose, prefilled syringes containing a 0.5‑mL suspension for injection. (3)

4 CONTRAINDICATIONS

- Severe allergic reaction (e.g., anaphylaxis) after a previous dose of any diphtheria toxoid-, tetanus toxoid-, pertussis- or poliovirus-containing vaccine, or to any component of KINRIX, including neomycin and polymyxin B. (4.1)
- Encephalopathy within 7 days of administration of a previous pertussis-containing vaccine. (4.2)
- Progressive neurologic disorders. (4.3)

5 WARNINGS AND PRECAUTIONS

- If Guillain-Barré syndrome occurs within 6 weeks of receipt of a prior vaccine containing tetanus toxoid, the decision to give KINRIX should be based on potential benefits and risks. (5.1)
- Syncope (fainting) can occur in association with administration of injectable vaccines, including KINRIX. Procedures should be in place to avoid falling injury and to restore cerebral perfusion following syncope. (5.2)
- If temperature ≥105°F, collapse or shock-like state, or persistent, inconsolable crying lasting ≥3 hours have occurred within 48 hours after receipt of a pertussis-containing vaccine, or if seizures have occurred within 3 days after receipt of a pertussis-containing vaccine, the decision to give KINRIX should be based on potential benefits and risks. (5.3)
- For children at higher risk for seizures, an antipyretic may be administered at the time of vaccination with KINRIX. (5.4)

6 ADVERSE REACTIONS

- The most frequently reported solicited local reaction (>50%) was injection site pain. Other common solicited local reactions (≥25%) were redness, increase in arm circumference, and swelling. (6.1)
- Common solicited general adverse reactions (≥15%) were drowsiness, fever (≥99.5°F), and loss of appetite. (6.1)

To report SUSPECTED ADVERSE REACTIONS, contact GlaxoSmithKline at 1-888-825-5249 or VAERS at 1-800-822-7967 or www.vaers.hhs.gov.

7 DRUG INTERACTIONS

Do not mix KINRIX with any other vaccine in the same syringe. (7.1)

FULL PRESCRIBING INFORMATION

1 INDICATIONS AND USAGE

A single dose of KINRIX is indicated for active immunization against diphtheria, tetanus, pertussis, and poliomyelitis as the fifth dose in the diphtheria, tetanus, and acellular pertussis (DTaP) vaccine series and the fourth dose in the inactivated poliovirus vaccine (IPV) series in children aged 4 through 6 years (prior to the seventh birthday) whose previous DTaP vaccine doses have been with INFANRIX (Diphtheria and Tetanus Toxoids and Acellular Pertussis Vaccine Adsorbed) and/or PEDIARIX [Diphtheria and Tetanus Toxoids and Acellular Pertussis Adsorbed, Hepatitis B (Recombinant) and Inactivated Poliovirus Vaccine] for the first 3 doses and INFANRIX for the fourth dose.

2 DOSAGE AND ADMINISTRATION

2.1 Preparation for Administration

Shake vigorously to obtain a homogeneous, turbid, white suspension. Do not use if resuspension does not occur with vigorous shaking. Parenteral drug products should be inspected visually for particulate matter and discoloration prior to administration, whenever solution and container permit. If either of these conditions exists, the vaccine should not be administered.

Attach a sterile needle and administer intramuscularly.

Do not administer this product intravenously, intradermally, or subcutaneously.

2.2 Recommended Dose and Schedule

KINRIX is to be administered as a 0.5-mL dose by intramuscular injection. The preferred site of administration is the deltoid muscle of the upper arm.

KINRIX may be used for the fifth dose in the DTaP immunization series and the fourth dose in the IPV immunization series in children aged 4 through 6 years (prior to the seventh birthday) whose previous DTaP vaccine doses have been with INFANRIX and/or PEDIARIX for the first 3 doses and INFANRIX for the fourth dose [see Indications and Usage (1)].

3 DOSAGE FORMS AND STRENGTHS

KINRIX is a suspension for injection available in 0.5-mL single-dose prefilled TIP‑LOK syringes.

4 CONTRAINDICATIONS

4.1 Hypersensitivity

Severe allergic reaction (e.g., anaphylaxis) after a previous dose of any diphtheria toxoid-, tetanus toxoid-, pertussis- or poliovirus-containing vaccine, or to any component of KINRIX, including neomycin and polymyxin B, is a contraindication to administration of KINRIX [see Description (11)]. Because of the uncertainty as to which component of the vaccine might be responsible, no further vaccination with any of these components should be given. Alternatively, such individuals may be referred to an allergist for evaluation if immunization with any of these components is considered.

4.2 Encephalopathy

Encephalopathy (e.g., coma, decreased level of consciousness, prolonged seizures) within 7 days of administration of a previous dose of a pertussis-containing vaccine that is not attributable to another identifiable cause is a contraindication to administration of any pertussis-containing vaccine, including KINRIX.

4.3 Progressive Neurologic Disorder

Progressive neurologic disorder, including infantile spasms, uncontrolled epilepsy, or progressive encephalopathy, is a contraindication to administration of any pertussis-containing vaccine, including KINRIX. Pertussis vaccine should not be administered to individuals with such conditions until a treatment regimen has been established and the condition has stabilized.

5 WARNINGS AND PRECAUTIONS

5.1 Guillain-Barré Syndrome

If Guillain-Barré syndrome occurs within 6 weeks of receipt of a prior vaccine containing tetanus toxoid, the decision to give any tetanus toxoid-containing vaccine, including KINRIX, should be based on careful consideration of the potential benefits and possible risks. When a decision is made to withhold tetanus toxoid, other available vaccines should be given, as indicated.

5.2 Syncope

Syncope (fainting) can occur in association with administration of injectable vaccines, including KINRIX. Syncope can be accompanied by transient neurological signs such as visual disturbance, paresthesia, and tonic-clonic limb movements. Procedures should be in place to avoid falling injury and to restore cerebral perfusion following syncope.

5.3 Adverse Reactions following Prior Pertussis Vaccination

If any of the following reactions occur in temporal relation to receipt of a pertussis-containing vaccine, the decision to give any pertussis-containing vaccine, including KINRIX, should be based on careful consideration of the potential benefits and possible risks:

- Temperature of ≥40.5oC (105oF) within 48 hours not due to another identifiable cause;
- Collapse or shock-like state (hypotonic-hyporesponsive episode) within 48 hours;
- Persistent, inconsolable crying lasting ≥3 hours, occurring within 48 hours;
- Seizures with or without fever occurring within 3 days.

When a decision is made to withhold pertussis vaccination, other available vaccines should be given, as indicated.

5.4 Children at Risk for Seizures

For children at higher risk for seizures than the general population, an appropriate antipyretic may be administered at the time of vaccination with a pertussis-containing vaccine, including KINRIX, and for the ensuing 24 hours to reduce the possibility of post-vaccination fever.

5.5 Preventing and Managing Allergic Vaccine Reactions

Prior to administration, the healthcare provider should review the patient’s immunization history for possible vaccine sensitivity and previous vaccination-related adverse reactions to allow an assessment of benefits and risks. Epinephrine and other appropriate agents used for the control of immediate allergic reactions must be immediately available should an acute anaphylactic reaction occur.

6 ADVERSE REACTIONS

6.1 Clinical Trials Experience

Because clinical trials are conducted under widely varying conditions, adverse reaction rates observed in the clinical trials of a vaccine cannot be directly compared with rates in the clinical trials of another vaccine and may not reflect the rates observed in practice.

A total of 4,013 children were vaccinated with a single dose of KINRIX in 4 clinical trials. Of these, 381 children received a non-U.S. formulation of KINRIX (containing ≤2.5 mg 2‑phenoxyethanol per dose as preservative).

The primary study (Study 048), conducted in the United States, was a randomized, controlled clinical trial in which children aged 4 to 6 years were vaccinated with KINRIX (n = 3,156) or control vaccines (INFANRIX and IPOL vaccine [IPV, Sanofi Pasteur SA]; n = 1,053) as a fifth DTaP vaccine dose following 4 doses of INFANRIX and as a fourth IPV dose following 3 doses of IPOL. Subjects also received the second dose of U.S.‑licensed measles, mumps, and rubella (MMR) vaccine (Merck & Co., Inc.) administered concomitantly, at separate sites.

Data on adverse events were collected by parents/guardians using standardized forms for 4 consecutive days following vaccination with KINRIX or control vaccines (i.e., day of vaccination and the next 3 days). The reported frequencies of solicited local reactions and general adverse reactions in Study 048 are presented in Table 1.

In 3 studies (Studies 046, 047, and 048), children were monitored for unsolicited adverse events, including serious adverse events that occurred in the 31-day period following vaccination, and in 2 studies (Studies 047 and 048), parents/guardians were actively queried about changes in the child’s health status, including the occurrence of serious adverse events, through 6 months post-vaccination.

Table 1. Percentage of Children Aged 4 to 6 Years Reporting Solicited Local or General Adverse Reactions within 4 Days of Vaccinationa with KINRIX or Separate Concomitant Administration of INFANRIX and IPV when Coadministered with MMR Vaccine (Study 048) (Total Vaccinated Cohort)
Adverse Reaction | KINRIX | INFANRIX + IPV
Localb | n = 3,121-3,128 | n = 1,039-1,043
Pain, any | 57c | 53
Pain, Grade 2 or 3d | 14 | 12
Pain, Grade 3d | 2c | 1
Redness, any | 37 | 37
Redness, ≥50 mm | 18 | 20
Redness, ≥110 mm | 3 | 4
Arm circumference increase, any | 36 | 38
Arm circumference increase, >20 mm | 7 | 7
Arm circumference increase, >30 mm | 2 | 3
Swelling, any | 26 | 27
Swelling, ≥50 mm | 10 | 12
Swelling, ≥110 mm | 1 | 2
General | n = 3,037-3,120 | n = 993-1,036
Drowsiness, any | 19 | 18
Drowsiness, Grade 3e | 1 | 1
Fever, ≥99.5°F | 16 | 15
Fever, >100.4°F | 7c | 4
Fever, >102.2°F | 1 | 1
Fever, >104°F | 0 | 0
Loss of appetite, any | 16 | 16
Loss of appetite, Grade 3f | 1 | 1
IPV = Inactivated poliovirus vaccine (Sanofi Pasteur SA); MMR = Measles, mumps, and rubella vaccine (Merck & Co., Inc.).
Total Vaccinated Cohort = All vaccinated subjects for whom safety data were available.
n = Number of children with evaluable data for the reactions listed.
a Within 4 days of vaccination defined as day of vaccination and the next 3 days.
b Local reactions at the injection site for KINRIX or INFANRIX.
c Statistically higher than comparator group (P <0.05).
d Grade 2 defined as painful when the limb was moved; Grade 3 defined as preventing normal daily activities.
e Grade 3 defined as preventing normal daily activities.
f Grade 3 defined as not eating at all.

In Study 048, KINRIX was non-inferior to INFANRIX with regard to swelling that involved >50% of the injected upper arm length and that was associated with a >30 mm increase in mid-upper arm circumference within 4 days following vaccination (upper limit of 2-sided 95% Confidence Interval for difference in percentage of KINRIX [0.6%, n = 20] minus INFANRIX [1.0%, n = 11] ≤2%).

Serious Adverse Events

Within the 31-day period following study vaccination in 3 studies (Studies 046, 047, and 048) in which all subjects received concomitant MMR vaccine (U.S.‑licensed MMR vaccine [Merck & Co., Inc.] in Studies 047 and 048, non—U.S.-licensed MMR vaccine in Study 046), 3 subjects (0.1% [3/3,537]) who received KINRIX reported serious adverse events (dehydration and hypernatremia; cerebrovascular accident; dehydration and gastroenteritis) and 4 subjects (0.3% [4/1,434]) who received INFANRIX and inactivated poliovirus vaccine (Sanofi Pasteur SA) reported serious adverse events (cellulitis, constipation, foreign body trauma, fever without identified etiology).

6.2 Postmarketing Experience

In addition to reports in clinical trials for KINRIX, the following adverse reactions have been identified during postapproval use of KINRIX. Because these reactions are reported voluntarily from a population of uncertain size, it is not always possible to reliably estimate their frequency or establish a causal relationship to vaccination.

General Disorders and Administration Site Conditions

Injection site vesicles.

Nervous System Disorders

Syncope.

Skin and Subcutaneous Tissue Disorders

Pruritus.

Additional adverse reactions reported following postmarketing use of INFANRIX, for which a causal relationship to vaccination is plausible, are: Allergic reactions, including anaphylactoid reactions, anaphylaxis, angioedema, and urticaria; apnea; collapse or shock-like state (hypotonic-hyporesponsive episode); convulsions (with or without fever); lymphadenopathy; and thrombocytopenia.

7 DRUG INTERACTIONS

7.1 Concomitant Vaccine Administration

In U.S. clinical trials, KINRIX was administered concomitantly with the second dose of MMR vaccine (Merck & Co., Inc.); in one of these trials (Study 055), KINRIX was also administered concomitantly with varicella vaccine (Merck & Co., Inc.) [see Clinical Studies (14.2)].

When KINRIX is administered concomitantly with other injectable vaccines, they should be given with separate syringes. KINRIX should not be mixed with any other vaccine in the same syringe.

7.2 Immunosuppressive Therapies

Immunosuppressive therapies, including irradiation, antimetabolites, alkylating agents, cytotoxic drugs, and corticosteroids (used in greater than physiologic doses), may reduce the immune response to KINRIX.

8 USE IN SPECIFIC POPULATIONS

8.4 Pediatric Use

Safety and effectiveness of KINRIX in children younger than 4 years and children aged 7 to 16 years have not been evaluated. KINRIX is not approved for use in persons in these age groups.

11 DESCRIPTION

KINRIX (Diphtheria and Tetanus Toxoids and Acellular Pertussis Adsorbed and Inactivated Poliovirus Vaccine) is a noninfectious, sterile vaccine for intramuscular administration. Each 0.5-mL dose is formulated to contain 25 Lf of diphtheria toxoid, 10 Lf of tetanus toxoid, 25 mcg of inactivated pertussis toxin (PT), 25 mcg of filamentous hemagglutinin (FHA), 8 mcg of pertactin (69 kiloDalton outer membrane protein), 40 D-antigen Units (DU) of Type 1 poliovirus (Mahoney), 8 DU of Type 2 poliovirus (MEF-1), and 32 DU of Type 3 poliovirus (Saukett). The diphtheria, tetanus, and pertussis components of KINRIX are the same as those in INFANRIX and PEDIARIX and the poliovirus component is the same as that in PEDIARIX.

The diphtheria toxin is produced by growing Corynebacterium diphtheriae (C. diphtheriae) in Fenton medium containing a bovine extract. Tetanus toxin is produced by growing Clostridium tetani (C. tetani) in a modified Latham medium derived from bovine casein. The bovine materials used in these extracts are sourced from countries which the United States Department of Agriculture (USDA) has determined neither have nor are at risk of bovine spongiform encephalopathy (BSE). Both toxins are detoxified with formaldehyde, concentrated by ultrafiltration, and purified by precipitation, dialysis, and sterile filtration.

The acellular pertussis antigens (PT, FHA, and pertactin) are isolated from Bordetella pertussis (B. pertussis) culture grown in modified Stainer-Scholte liquid medium. PT and FHA are isolated from the fermentation broth; pertactin is extracted from the cells by heat treatment and flocculation. The antigens are purified in successive chromatographic and precipitation steps. PT is detoxified using glutaraldehyde and formaldehyde. FHA and pertactin are treated with formaldehyde.

Diphtheria and tetanus toxoids and pertussis antigens (inactivated PT, FHA, and pertactin) are individually adsorbed onto aluminum hydroxide.

The inactivated poliovirus component of KINRIX is an enhanced potency component. Each of the 3 strains of poliovirus is individually grown in VERO cells, a continuous line of monkey kidney cells, cultivated on microcarriers. Calf serum and lactalbumin hydrolysate are used during VERO cell culture and/or virus culture. Calf serum is sourced from countries the USDA has determined neither have nor are at risk of BSE. After clarification, each viral suspension is purified by ultrafiltration, diafiltration, and successive chromatographic steps, and inactivated with formaldehyde. The 3 purified viral strains are then pooled to form a trivalent concentrate.

Diphtheria and tetanus toxoid potency is determined by measuring the amount of neutralizing antitoxin in previously immunized guinea pigs. The potency of the acellular pertussis components (inactivated PT, FHA, and pertactin) is determined by enzyme-linked immunosorbent assay (ELISA) on sera from previously immunized mice. The potency of the inactivated poliovirus component is determined by using the D-antigen ELISA and by a poliovirus-neutralizing cell culture assay on sera from previously immunized rats.

Each 0.5-mL dose contains aluminum hydroxide as adjuvant (formulated to contain 0.5 mg aluminum) and ≤4.4 mg of sodium chloride. The aluminum content is measured by assay. Each dose also contains ≤100 mcg of residual formaldehyde and ≤100 mcg of polysorbate 80 (Tween 80). Neomycin sulfate and polymyxin B sulfate are used in the poliovirus vaccine manufacturing process and may be present in the final vaccine at ≤0.05 ng neomycin and ≤0.01 ng polymyxin B per dose.

The tip cap and rubber plunger stopper of the prefilled syringe are not made with natural rubber latex.

KINRIX does not contain a preservative.

12 CLINICAL PHARMACOLOGY

12.1 Mechanism of Action

Diphtheria

Diphtheria is an acute toxin-mediated infectious disease caused by toxigenic strains of C. diphtheriae. Protection against disease is due to the development of neutralizing antibodies to the diphtheria toxin. A serum diphtheria antitoxin level of 0.01 IU/mL is the lowest level giving some degree of protection; a level of 0.1 IU/mL is regarded as protective.^1

Tetanus

Tetanus is an acute toxin-mediated disease caused by a potent exotoxin released by C. tetani. Protection against disease is due to the development of neutralizing antibodies to the tetanus toxin. A serum tetanus antitoxin level of at least 0.01 IU/mL, measured by neutralization assays, is considered the minimum protective level.^2,3 A level of ≥0.1 IU/mL is considered protective.^4

Pertussis

Pertussis (whooping cough) is a disease of the respiratory tract caused by B. pertussis. The role of the different components produced by B. pertussis in either the pathogenesis of, or the immunity to, pertussis is not well understood. There is no well-established serological correlate of protection for pertussis. The efficacy of the pertussis component of KINRIX was determined in clinical trials of INFANRIX administered as a 3-dose series in infants (see INFANRIX prescribing information).

Poliomyelitis

Poliovirus is an enterovirus that belongs to the picornavirus family. Three serotypes of poliovirus have been identified (Types 1, 2, and 3). Neutralizing antibodies against the 3 poliovirus serotypes are recognized as conferring protection against poliomyelitis disease.^5

13 NONCLINICAL TOXICOLOGY

13.1 Carcinogenesis, Mutagenesis, Impairment of Fertility

KINRIX has not been evaluated for carcinogenic or mutagenic potential or for impairment of fertility.

14 CLINICAL STUDIES

14.1 Immunological Evaluation

In a U.S. multicenter study (Study 048), 4,209 children were randomized in a 3:1 ratio to receive either KINRIX or INFANRIX and IPV (Sanofi Pasteur SA) administered concomitantly at separate sites. Subjects also received MMR vaccine (Merck & Co., Inc.) administered concomitantly at a separate site. Subjects were children aged 4 through 6 years who previously received 4 doses of INFANRIX, 3 doses of IPV, and 1 dose of MMR vaccine. Among subjects in both vaccine groups combined, 49.6% were female; 45.6% of subjects were White, 18.8% Hispanic, 13.6% Asian, 7.0% Black, and 15.0% were of other racial/ethnic groups.

Levels of antibodies to the diphtheria, tetanus, pertussis (PT, FHA, and pertactin), and poliovirus antigens were measured in sera obtained immediately prior to vaccination and 1 month (range: 31 to 48 days) after vaccination (Table 2). The co-primary immunogenicity endpoints were anti-diphtheria toxoid, anti-tetanus toxoid, anti-PT, anti-FHA, and anti-pertactin booster responses, and anti-poliovirus Type 1, Type 2, and Type 3 geometric mean antibody titers (GMTs) 1 month after vaccination. KINRIX was shown to be non-inferior to INFANRIX and IPV administered separately, in terms of booster responses to DTaP antigens and post-vaccination GMTs for anti-poliovirus antibodies (Table 2).

Table 2. Pre-Vaccination Antibody Levels and Post-Vaccinationa Antibody Responses following KINRIX Compared with Separate Concomitant Administration of INFANRIX and IPV in Children Aged 4 to 6 Years when Coadministered with MMR Vaccine (Study 048) (ATP Cohort for Immunogenicity)
 | KINRIX | INFANRIX + IPV
 | n = 787-851 | n = 237-262
Anti‑diphtheria Toxoid
Pre-vaccination % ≥0.1 IU/mL (95% CI)b | 87.7 (85.3, 89.9) | 85.5 (80.6, 89.5)
Post-vaccination % ≥0.1 IU/mL (95% CI)b | 100 (99.6, 100) | 100 (98.6, 100)
% Booster Response (95% CI)c | 99.5 (98.8, 99.9)d | 100 (98.6, 100)
Anti‑tetanus Toxoid
Pre-vaccination % ≥0.1 IU/mL (95% CI)b | 87.8 (85.4, 90.0) | 88.2 (83.6, 91.8)
Post-vaccination % ≥0.1 IU/mL (95% CI)b | 100 (99.6, 100) | 100 (98.6, 100)
% Booster Response (95% CI)c | 96.7 (95.2, 97.8)d | 93.9 (90.2, 96.5)
Anti‑PT
% Booster Response (95% CI)e | 92.2 (90.2, 94.0)d | 92.6 (88.7, 95.5)
Anti‑FHA
% Booster Response (95% CI)e | 95.4 (93.7, 96.7)d | 96.2 (93.1, 98.1)
Anti‑pertactin
% Booster Response (95% CI)e | 97.8 (96.5, 98.6)d | 96.9 (94.1, 98.7)
Anti‑poliovirus 1
Pre-vaccination % ≥1:8 (95% CI)b | 88.3 (85.9, 90.4) | 85.1 (80.1, 89.2)
Post-vaccination % ≥1:8 (95% CI)b | 99.9 (99.3, 100) | 100 (98.5, 100)
Post-vaccination GMT (95% CI) | 2,127 (1,976, 2,290)f | 1,685 (1,475, 1,925)
Anti‑poliovirus 2
Pre-vaccination % ≥1:8 (95% CI)b | 91.8 (89.7, 93.6) | 87.0 (82.3, 90.8)
Post-vaccination % ≥1:8 (95% CI)b | 100 (99.6, 100) | 100 (98.5, 100)
Post-vaccination GMT (95% CI) | 2,265 (2,114, 2,427)f | 1,818 (1,606, 2,057)
Anti‑poliovirus 3
Pre-vaccination % ≥1:8 (95% CI)b | 84.7 (82.0, 87.0) | 85.0 (80.1, 89.1)
Post-vaccination % ≥1:8 (95% CI)b | 100 (99.5, 100) | 100 (98.5, 100)
Post-vaccination GMT (95% CI) | 3,588 (3,345, 3,849)f | 3,365 (2,961, 3,824)
ATP = According-to-protocol; CI = Confidence Interval; GMT = Geometric mean antibody titer; IPV = Inactivated poliovirus vaccine (Sanofi Pasteur SA); MMR = Measles, mumps, and rubella vaccine (Merck & Co., Inc.).
n = Number of subjects with available results.
a One-month blood sampling, range 31 to 48 days.
b Seroprotection defined as anti-diphtheria toxoid and anti-tetanus toxoid antibody concentrations ≥0.1 IU/mL by ELISA and as anti-poliovirus Type 1, Type 2, and Type 3 antibody titer ≥1:8 by micro-neutralization assay for poliovirus.
c Booster response: In subjects with pre-vaccination <0.1 IU/mL, post-vaccination concentration ≥0.4 IU/mL. In subjects with pre-vaccination concentration ≥0.1 IU/mL, an increase of at least 4 times the pre-vaccination concentration.
d KINRIX was non-inferior to INFANRIX + IPV based on booster response rates (upper limit of 2-sided 95% CI on the difference of INFANRIX + IPV minus KINRIX ≤10%).
e Booster response: In subjects with pre-vaccination <5 EL.U./mL, post-vaccination concentration ≥20 EL.U./mL. In subjects with pre-vaccination ≥5 EL.U./mL and <20 EL.U./mL, an increase of at least 4 times the pre-vaccination concentration. In subjects with pre-vaccination ≥20 EL.U./mL, an increase of at least 2 times the pre-vaccination concentration.
f KINRIX was non-inferior to INFANRIX + IPV based on post-vaccination anti-poliovirus antibody GMTs adjusted for baseline titer (upper limit of 2-sided 95% CI for the GMT ratio [INFANRIX + IPV:KINRIX] ≤1.5).

14.2 Concomitant Vaccine Administration

In a U.S. study (Study 055) that enrolled children aged 4 to 6 years, KINRIX was administered concomitantly at separate sites with MMR vaccine (Merck & Co., Inc.) (n = 237) or with MMR vaccine and varicella vaccine (Merck & Co., Inc.) (n = 239). Immune responses to the antigens contained in KINRIX were measured approximately 1 month (28 to 48 days) after vaccination. Booster responses to diphtheria, tetanus, and pertussis antigens and GMTs for poliovirus (Type 1, 2, and 3) after the receipt of KINRIX administered concomitantly with MMR vaccine and varicella vaccine were non-inferior to immune responses following concomitant administration of KINRIX administered with MMR vaccine.

15 REFERENCES

1. Vitek CR and Wharton M. Diphtheria Toxoid. In: Plotkin SA, Orenstein WA, and Offit PA, eds. Vaccines. 5th ed. Saunders; 2008:139-156.
2. Wassilak SGF, Roper MH, Kretsinger K, and Orenstein WA. Tetanus Toxoid. In: Plotkin SA, Orenstein WA, and Offit PA, eds. Vaccines. 5th ed. Saunders; 2008:805-839.
3. Department of Health and Human Services, Food and Drug Administration. Biological products; Bacterial vaccines and toxoids; Implementation of efficacy review; Proposed rule. Federal Register. December 13, 1985;50(240):51002-51117.
4. Centers for Disease Control and Prevention. General Recommendations on Immunization. Recommendations of the Advisory Committee on Immunization Practices (ACIP). MMWR. 2006;55(RR-15):1-48.
5. Sutter RW, Pallansch MA, Sawyer LA, et al. Defining surrogate serologic tests with respect to predicting protective vaccine efficacy: Poliovirus vaccination. In: Williams JC, Goldenthal KL, Burns DL, Lewis Jr BP, eds. Combined vaccines and simultaneous administration. Current issues and perspectives. New York, NY: The New York Academy of Sciences; 1995:289-299.

16 HOW SUPPLIED/STORAGE AND HANDLING

KINRIX is available in 0.5-mL single-dose, disposable, prefilled TIP‑LOK syringes (Luer Lock syringes) packaged without needles. TIP-LOK syringes are to be used with Luer Lock compatible needles. The tip cap and rubber plunger stopper of the prefilled syringe are not made with natural rubber latex.

NDC 58160-812-43 Syringe in Package of 10: NDC 58160-812-52

Store refrigerated between 2° and 8°C (36° and 46°F). Do not freeze. Discard if the vaccine has been frozen.

17 PATIENT COUNSELING INFORMATION

Provide the following information to the parent or guardian:

- Inform of the potential benefits and risks of immunization with KINRIX.
- Inform about the potential for adverse reactions that have been temporally associated with administration of KINRIX or other vaccines containing similar components.
- Give the Vaccine Information Statements, which are required by the National Childhood Vaccine Injury Act of 1986 to be given prior to immunization. These materials are available free of charge at the Centers for Disease Control and Prevention (CDC) website (www.cdc.gov/vaccines).

INFANRIX, KINRIX, PEDIARIX, and TIP‑LOK are trademarks owned by or licensed to the GSK group of companies. The other brand listed is a trademark owned by or licensed to its respective owner and is not owned by or licensed to the GSK group of companies. The maker of this brand is not affiliated with and does not endorse the GSK group of companies or its products.

Manufactured by GlaxoSmithKline Biologicals

Rixensart, Belgium, U.S. License 1617, and

GSK Vaccines GmbH

Marburg, Germany, U.S. License 1617

Distributed by GlaxoSmithKline

Durham, NC 27701

©2024 GSK group of companies or its licensor.

KNX:19PI

PACKAGE LABEL

PRINCIPAL DISPLAY PANEL

NDC 58160-812-52

KINRIX

Diphtheria and Tetanus Toxoids and Acellular Pertussis Adsorbed and Inactivated Poliovirus Vaccine

DTaP-IPV

Rx only

For Use from 4 through 6 Years of Age

10 Disposable Single-Dose Prefilled TIP-LOK Syringes each containing one 0.5-mL dose

TIP-LOK syringes to be used with Luer-Lok compatible needles

NEEDLES NOT INCLUDED

GSK

Kinrix

KINRIX and TIP-LOK are trademarks owned by or licensed to the GSK group of companies.

LUER-LOK is a trademark owned by or licensed to Becton, Dickinson, and Company.

Made in Belgium

©2023 GSK group of companies or its licensor.

Rev. 10/23

516605